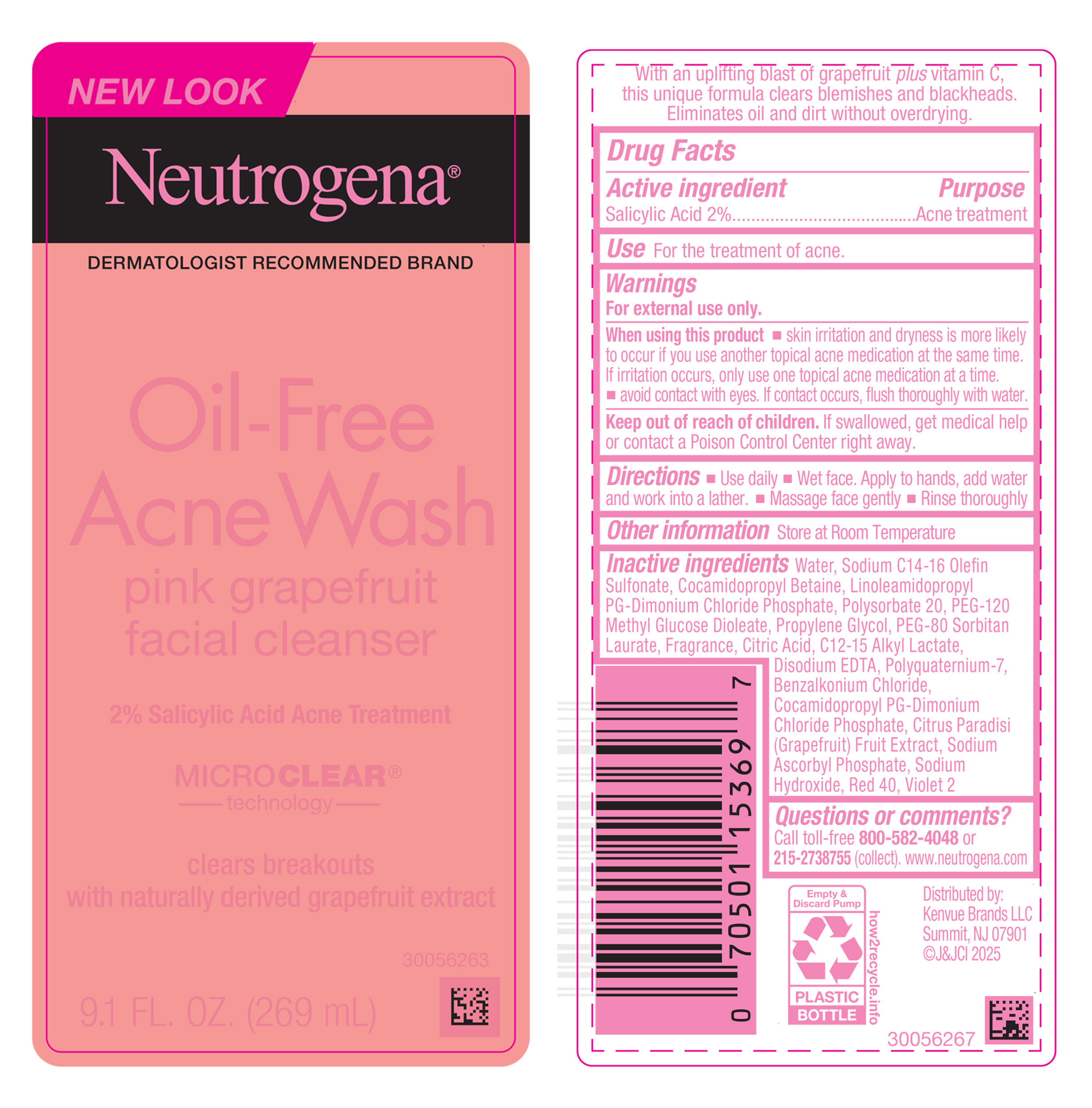 DRUG LABEL: Neutrogena Oil Free Acne Wash Pink Grapefruit Facial Cleanser
NDC: 69968-0926 | Form: LIQUID
Manufacturer: Kenvue Brands LLC
Category: otc | Type: HUMAN OTC DRUG LABEL
Date: 20250516

ACTIVE INGREDIENTS: SALICYLIC ACID 20 mg/1 mL
INACTIVE INGREDIENTS: GRAPEFRUIT; WATER; SODIUM C14-16 OLEFIN SULFONATE; COCAMIDOPROPYL BETAINE; LINOLEAMIDOPROPYL PROPYLENE GLYCOL-DIMONIUM CHLORIDE PHOSPHATE; PEG-80 SORBITAN LAURATE; POLYSORBATE 20; PEG-120 METHYL GLUCOSE DIOLEATE; PROPYLENE GLYCOL; CITRIC ACID MONOHYDRATE; C12-15 ALKYL LACTATE; EDETATE DISODIUM; BENZALKONIUM CHLORIDE; POLYQUATERNIUM-7 (70/30 ACRYLAMIDE/DADMAC; 1600000 MW); COCAMIDOPROPYL PROPYLENE GLYCOL-DIMONIUM CHLORIDE PHOSPHATE; SODIUM HYDROXIDE; FD&C RED NO. 40; D&C VIOLET NO. 2; SODIUM ASCORBYL PHOSPHATE

Neutrogena® Oil-Free Acne Wash pink grapefruit facial cleanser

Drug Facts

Active ingredient

Salicylic Acid 2%

Purpose

Acne treatment

Use

For the treatment of acne.

Warnings

For external use only.

When using this product

- skin irritation and dryness is more likely to occur if you use another topical acne medication at the same time. If irritation occurs, only use one topical acne medication at a time.
- avoid contact with eyes. If contact occurs, flush thoroughly with water.

Keep out of reach of children. If swallowed, get medical help or contact a Poison Control Center right away.

Directions

- Use daily
- Wet face. Apply to hands, add water and work into a lather.
- Massage face gently
- Rinse thoroughly.

Other information

Store at Room Temperature

Inactive ingredients

Water, Sodium C14-16 Olefin Sulfonate, Cocamidopropyl Betaine, Linoleamidopropyl PG-Dimonium Chloride Phosphate, Polysorbate 20, PEG-120 Methyl Glucose Dioleate, Propylene Glycol, PEG-80 Sorbitan Laurate, Fragrance, Citric Acid, C12-15 Alkyl Lactate, Disodium EDTA, Polyquaternium-7, Benzalkonium Chloride, Cocamidopropyl PG-Dimonium Chloride Phosphate, Citrus Paradisi (Grapefruit) Fruit Extract, Sodium Ascorbyl Phosphate, Sodium Hydroxide, Red 40, Violet 2

Questions or comments?

Call toll-free 800-582-4048 or 215-273-8755 (collect). www.neutrogena.com

Distributed by:

Kenvue Brands LLC

Summit, NJ 07901

PRINCIPAL DISPLAY PANEL - 269 mL Bottle Label

NEW LOOK

Neutrogena®

DERMATOLOGIST RECOMMENDED BRAND

Oil-Free

Acne Wash

pink grapefruit

facial cleanser

2% Salicylic Acid Acne Treatment

MICROCLEAR®

technology

clears breakouts

with naturally derived grapefruit extract

9.1 FL.OZ. (269 mL)